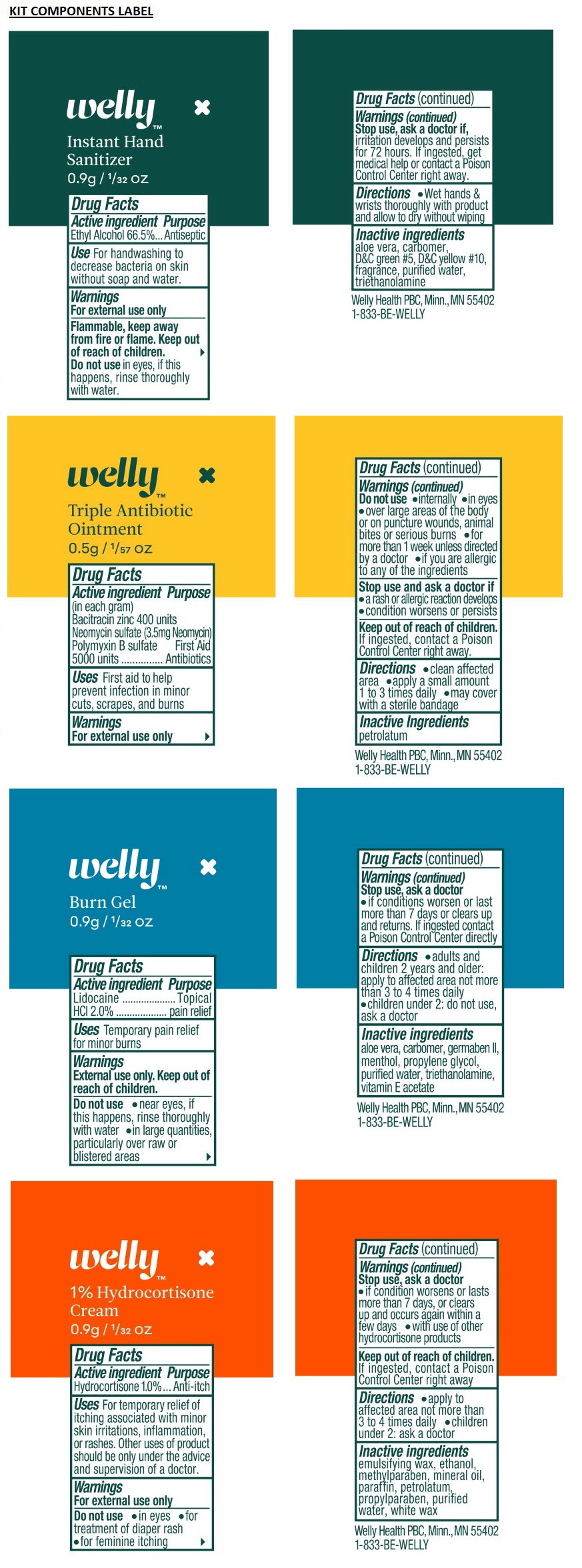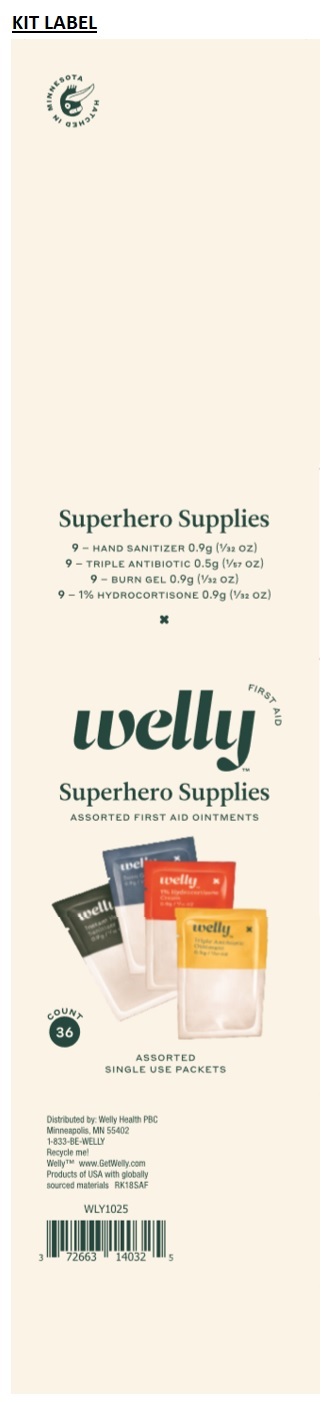 DRUG LABEL: Welly Superhero Supplies Kit
NDC: 72663-140 | Form: KIT | Route: TOPICAL
Manufacturer: Welly Health PBC
Category: otc | Type: HUMAN OTC DRUG LABEL
Date: 20211231

ACTIVE INGREDIENTS: ALCOHOL 666 mg/1 mL; BACITRACIN ZINC 6 mg/1 mL; NEOMYCIN SULFATE 3.5 mg/1 mL; POLYMYXIN B SULFATE 0.77 mg/1 mL; LIDOCAINE HYDROCHLORIDE 2 g/1 mL; HYDROCORTISONE 1 g/1 mL
INACTIVE INGREDIENTS: ALOE VERA LEAF; CARBOMER INTERPOLYMER TYPE A (ALLYL SUCROSE CROSSLINKED); D&C GREEN NO. 5; D&C YELLOW NO. 10; WATER; TROLAMINE; PETROLATUM; ALOE VERA LEAF; CARBOXYPOLYMETHYLENE; DIAZOLIDINYL UREA; MENTHOL, UNSPECIFIED FORM; PROPYLENE GLYCOL; WATER; TROLAMINE; .ALPHA.-TOCOPHEROL, D-; ALCOHOL; METHYLPARABEN; MINERAL OIL; PARAFFIN; PETROLATUM; PROPYLPARABEN; WATER; WHITE WAX

Welly Superhero Supplies Kit

Instant Hand Sanitizer Gel

Drug Facts

Active ingredient

Ethyl Alcohol 66.5%

Purpose

Antiseptic

Use

For handwashing to decrease bacteria on skin without soap and water.

Warnings

For external use only

Flammable, keep away from fire or flame.

Do not use in eyes, if this happens, rinse thoroughly with water.

Stop use, ask a doctor if, irritation develops and persists for 72 hours.

Keep out of reach of children. If ingested, get medical help or contact a Poison Control Center right away.

Directions

- Wet hands & wrists thoroughly with product and allow to dry without wiping

Inactive ingredients

aloe vera, carbomer, D&C green #5, D&C yellow #10, fragrance, purified water, triethanolamine

Triple Antibiotic Ointment

Drug Facts

Active Ingredient (in each gram)

Bacitracin zinc 400 units

Neomycin sulfate (3.5mg Neomycin)

Polymyxin B sulfate 5000 units

Purpose

First Aid Antibiotics

Uses

First aid to help prevent infection in minor cuts, scrapes and burns

Warnings

For external use only

Do not use:

- internally
- in eyes
- over large areas of the body or on puncture wounds, animal bites or serious burns
- for more than 1 week unless directed by a doctor
- if you are allergic to any of the ingredients

Stop use and ask a doctor if

- a rash or allergic reactions develops
- condition worsens or persists

Keep out of reach of children. If ingested, contact a Poison Control Center right away.

Directions

- clean affected area
- apply a small amount 1 to 3 times daily
- may cover with a sterile bandage

Inactive Ingredients

petrolatum

Burn Gel

Drug Facts

Active ingredient

Lidocaine HCl 2.0%

Purpose

Topical pain relief

Uses

Temporary pain relief for minor burns

Warnings

External use only

Do not use

- near eyes, if this happens, rinse thoroughly with water
- in large quantities, particularly over raw or blistered areas

Stop use, ask doctor

- if conditions worsen or last more than 7 days or clears up and returns.

Keep out of reach of children. If ingested contact a Poison Control Center directly

Directions

- adults and children 2 years and older: apply to affected area not more than 3 to 4 times daily
- children under 2: do not use, ask a doctor

Inactive ingredients

aloe vera, carbomer, germaben II, menthol, propylene glycol, purified water, triethanolamine, vitamin E acetate

1% Hydrocortisone Cream

Drug Facts

Active ingredient

Hydrocortisone 1.0%

Purpose

Anti-itch

Uses

- For temporary relief of itching associated with minor skin irritations, inflammation, or rashes.
- Other uses of product should be only under the advice and supervision of a doctor.

Warnings

For external use only

Do not use

- in eyes
- for treatment of diaper rash
- for feminine itching

Stop use, ask a doctor

- if condition worsens or lasts more than 7 days, or clears up and occurs again within a few days
- with use of other hydrocortisone products

Keep out of reach of children. If ingested, contact a Poison Control Center right away

Directions

- apply to affected area not more than 3 to 4 times daily
- children under 2: ask a doctor

Inactive ingredients

emulsifying wax, ethanol, methylparaben, mineral oil, paraffin, petrolatum, propylparaben, purified water, white wax

ASSORTED FIRST AID OINTMENTS

ASSORTED SINGLE USE PACKETS

Distributed by: Welly Health PBC
Minneapolis, MN 55402
1-833-BE-WELLY

Recycle me!

WellyTM www.GetWelly.com

Superhero Supplies

9 - HAND SANITIZER 0.9g (1/32 OZ)

9 - TRIPLE ANTIBIOTIC 0.5g (1/57 OZ)

9 - BURN GEL 0.9G (1/32 OZ)

9 - 1% HYDROCORTISONE 0.9g (1/32 OZ)